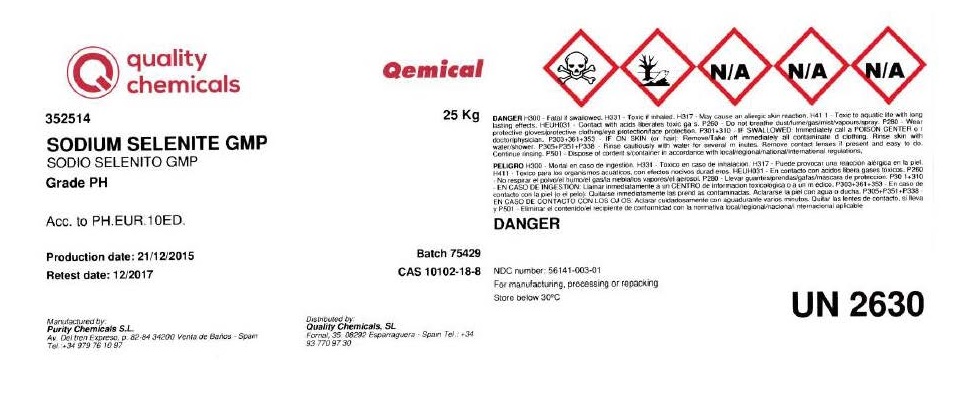 DRUG LABEL: Sodium Selenite
NDC: 56141-003 | Form: POWDER
Manufacturer: Quality Chemicals S.L.
Category: other | Type: BULK INGREDIENT - ANIMAL DRUG
Date: 20211130

ACTIVE INGREDIENTS: SODIUM SELENITE 1 kg/1 kg

Sodium Selenite